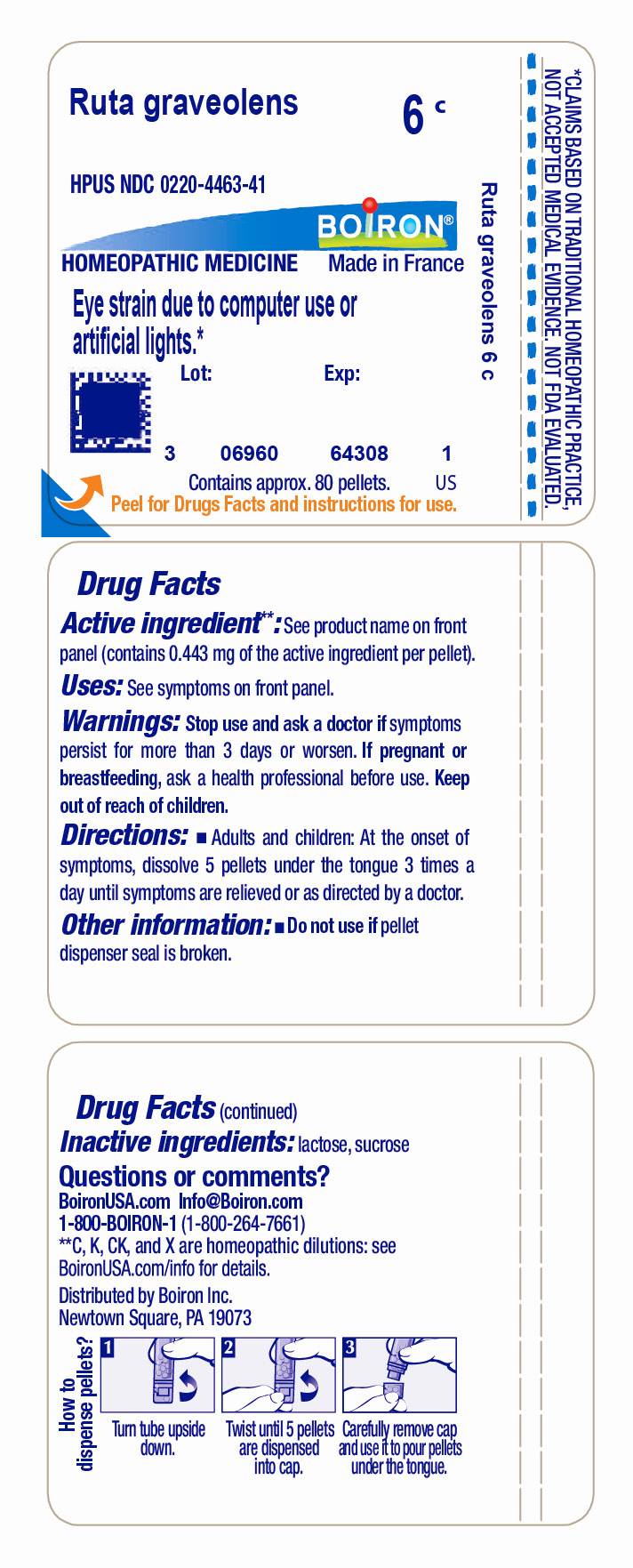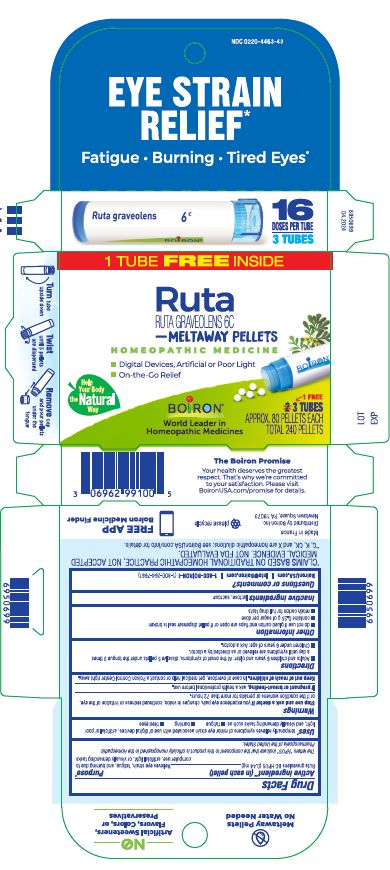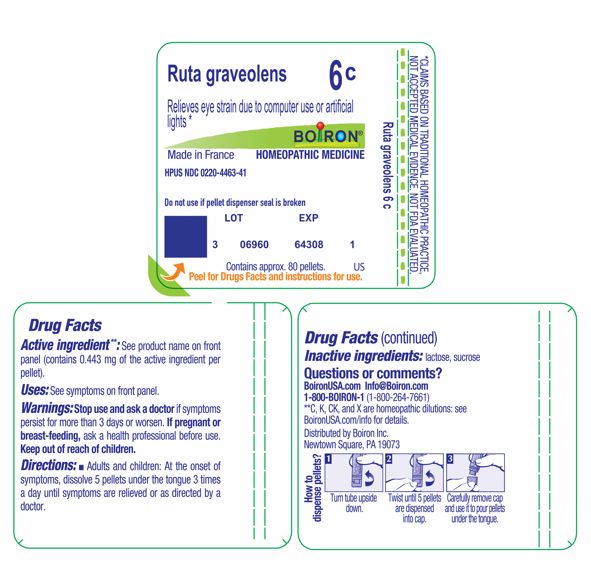 DRUG LABEL: Ruta graveolens
NDC: 0220-4463 | Form: PELLET
Manufacturer: Boiron
Category: homeopathic | Type: HUMAN OTC DRUG LABEL
Date: 20240611

ACTIVE INGREDIENTS: RUTA GRAVEOLENS FLOWERING TOP 6 [hp_C]/6 [hp_C]
INACTIVE INGREDIENTS: SUCROSE; LACTOSE, UNSPECIFIED FORM

Ruta graveolens 6C

Active ingredient** (in each pellet)

Ruta graveolens 6C HPUS
(** contains 0.44 mg of the active ingredient per pellet)

The letters "HPUS" indicate that the components in this product are officially monographed in the Homeopathic Pharmacopoeia of the United States.

PURPOSE

Relieves eye strain, fatigue, and burning due to computer use, artificial light, or visually demanding tasks

INDICATIONS AND USAGE

Eye Strain Relief Uses*

temporarily relieves symptoms of minor eye strain associated with use of digital devices, artificial or poor light, and visually demanding tasks such as:

- fatigue
- burning
- tired eyes

Tube Uses*

Relieves eye strain due to computer use or artificial lights *

STOP USE

Eye Strain Relief Carton

Stop use and ask a doctor if you experience eye pain, changes in vision, continued redness or irritation of the eye, or if the condition worsens or persists for more than 72 hours.

Tube

Stop use and ask a doctor if symptoms persist for more than 3 days or worsen.

PREGNANCY OR BREAST FEEDING

If pregnant or breast-feeding, ask a health professional before use.

Keep out of reach of children. In case of overdose, get medical help or contact a Poison Control Center right away.

DOSAGE AND ADMINISTRATION

Eye Strain Relief Carton

- Adults and children 6 years and older: At the onset of symptoms, dissolve 5 pellets under the tongue 3 times a day until symptoms are relieved or as directed by a doctor.
- Children under 6 years of age: Ask a doctor.

Tube

Adults and children: At the onset of symptoms, dissolve 5 pellets under the tongue 3 times a day until symptoms are relieved or as directed by a doctor.

INACTIVE INGREDIENT

lactose, sucrose

Eye Strain Relief Carton

Eye Strain Relief*

Fatique, Burning, Tired Eyes*

3 Tubes

16 Doses

Total 240 Pellets

do not use if glued carton end flaps are open or if pellet dispenser seal is broken

contains 0.25g of sugar per dose

retain carton for full drug facts

Turn tube upside down. Twist until 5 pellets are dispensed into cap. Carefully remove the cap and use it to pour pellets under the tongue.

Tube

Do not use if pellet dispenser seal is broken.
Contains approx 80 pellets.
How to dispense pellets? Turn tube upside down. Twist until 5 pellets are dispensed into cap. Carefully remove the cap and use it to pour pellets under the tongue.
*CLAIMS BASED ON TRADITIONAL HOMEOPATHIC PRACTICE NOT ACCEPTED MEDICAL EVIDENCE. NOT FDA EVALUATED.
*C,K,CK, and X are homeopathic dilutions: see BoironUSA.com/info for details.

QUESTIONS

BoironUSA.com Info@boiron.com
1-800-BOIRON-1 (1-800-264-7661)
Distributed by Boiron, Inc.
Newtown Square, PA 19073